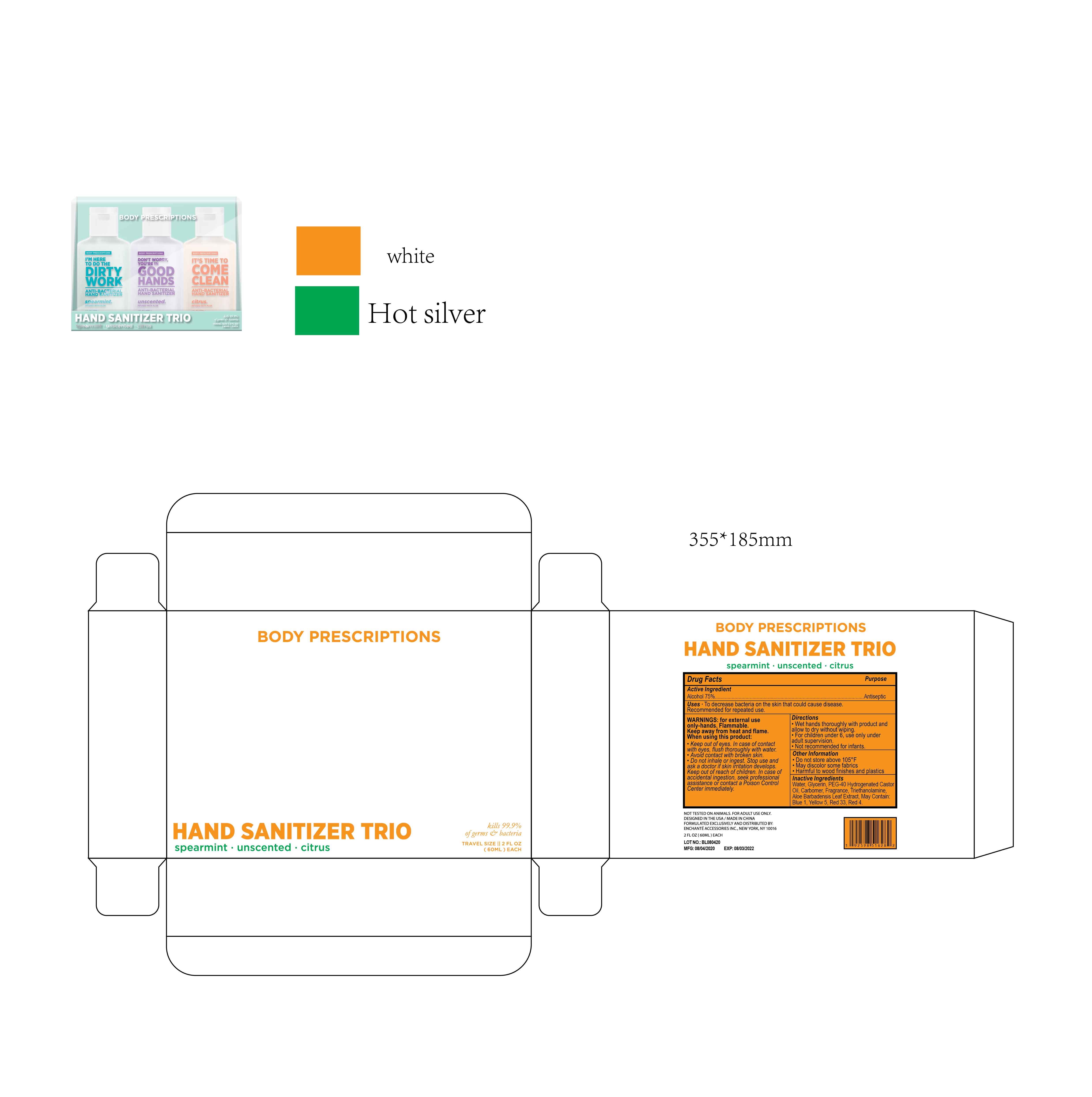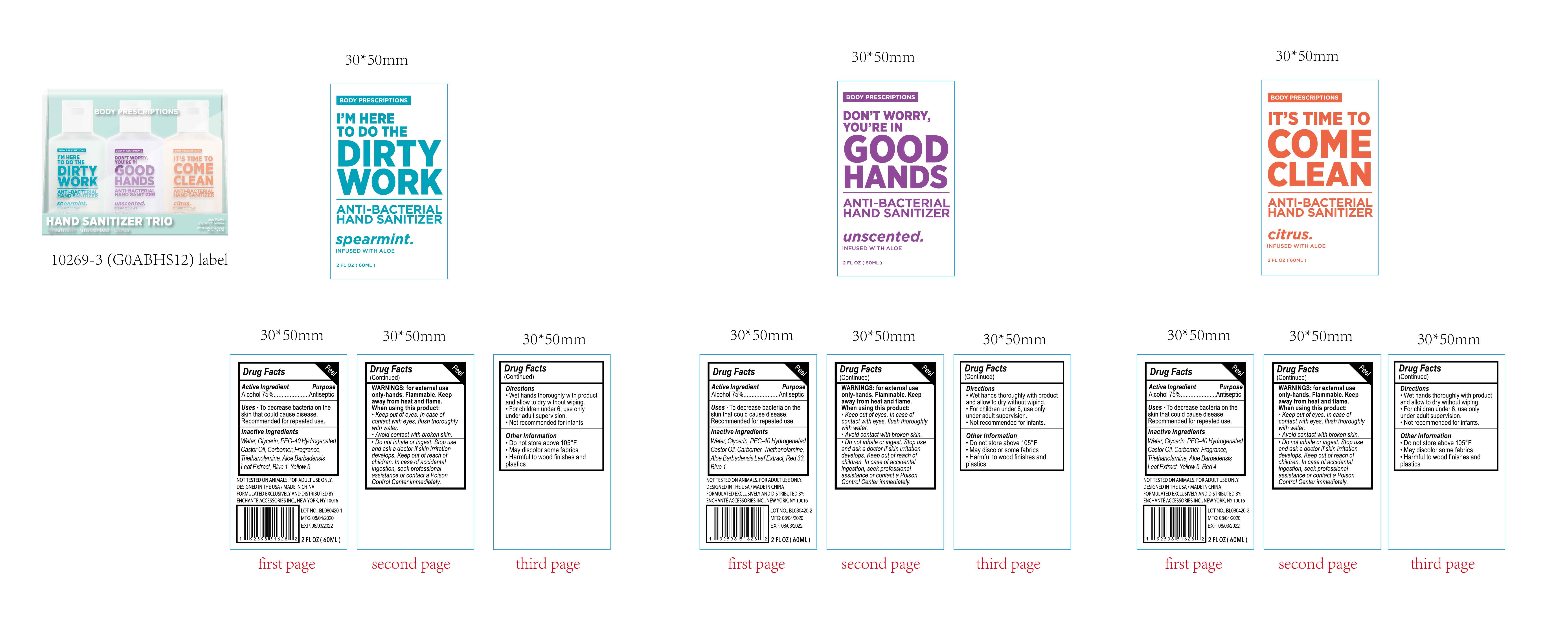 DRUG LABEL: BODY PRESCRIPTIONS HAND SANITIZER TRIO SPEARMINT UNSCENTED CITRUS
NDC: 50563-256 | Form: KIT | Route: TOPICAL
Manufacturer: ENCHANTE ACCESSORIES INC.
Category: otc | Type: HUMAN OTC DRUG LABEL
Date: 20200916

ACTIVE INGREDIENTS: ALCOHOL 75 mL/100 mL; ALCOHOL 75 mL/100 mL; ALCOHOL 75 mL/100 mL
INACTIVE INGREDIENTS: WATER; GLYCERIN; CARBOMER 940; TROLAMINE; ALOE VERA LEAF; FD&C BLUE NO. 1; FD&C YELLOW NO. 5; WATER; GLYCERIN; CARBOMER 940; TROLAMINE; ALOE VERA LEAF; FD&C BLUE NO. 1; D&C RED NO. 33; WATER; GLYCERIN; CARBOMER 940; TROLAMINE; ALOE VERA LEAF; FD&C YELLOW NO. 5; FD&C RED NO. 4

50563_253/254/255/256_G0ABHS12

BODY PRESCRIPTIONS ANTIBACTERIAL HAND SANITIZER Spearmint

Active Ingredient

Alcohol 75%

Purpose

Antiseptic

Use

■ To decrease bacteria on the skin that could cause disease
■Recommended for repeated use

WARNINGS

For external use only, Hands

Flammable. Keep away from heat and flame

When using this product, keep out of eyes.
In case of contact with eyes, flush thoroughly with water

Avoid contact with broken skin

Do not inhale or ingest

Stop Use

Stop use and ask a doctor if skin irritation develops

Keep out of reach of children. In case of accidental ingestion, seek professional assistance or contact a poison control center immediately

Directions

Wet hands thoroughly with product and allow to dry without wiping

For children under 6, use only under adult supervision

Not recommended for infants

Other information

Do not store above 105F

May discolor some fabrics

Harmful to wood finishes and plastics

Inactive ingredients

Water, Glycerin, PEG-40 Hydrogenated Castor Oil, Carbomer, Triethanolamine, Aloe Barbadensis Leaf Extract, Blue 1, Yellow 5

BODY PRESCRIPTIONS ANTIBACTERIAL HAND SANITIZER Unsented

BODY PRESCRIPTIONS ANTIBACTERIAL HAND SANITIZER Unscented

Active Ingredient

Alcohol 75%

Purpose:

Antiseptic

Uses:

To decrease bacteria on the skin that could cause disease
■Recommended for repeated use

Warnings

For external use only, Hands

Flammable. Keep away from heat and flame

When using this product, keep out of eyes.
In case of contact with eyes, flush thoroughly with water

Avoid contact with broken skin

Do not inhale or ingest

Stop Use

Stop use and ask a doctor if skin irritation develops

Keep out of reach of children. In case of accidental ingestion, seek professional assistance or contact a poison control center immediately

Directions

Wet hands thoroughly with product and allow to dry without wiping

For children under 6, use only under adult supervision

Not recommended for infants

Other Information

Do not store above 105F

May discolor some fabrics

Harmful to wood finishes and plastics

Inactive Ingredients

Water, Glycerin, PEG-40 Hydrogenated Castor Oil, Carbomer, Triethanolamine, Aloe Barbadensis Leaf Extract, Red 33, Blue 1

BODY PRESCRIPTIONS ANTIBACTERIAL HAND SANITIZER Citrus

Active Ingredient

Alcohol 75%

Purpose

Antiseptic

Uses

To decrease bacteria on the skin that could cause disease
■Recommended for repeated use

Warnings

For external use only, Hands

Flammable. Keep away from heat and flame

When using this product, keep out of eyes.
In case of contact with eyes, flush thoroughly with water

Avoid contact with broken skin

Do not inhale or ingest

Stop Use

Stop use and ask a doctor if skin irritation develops

Keep out of reach of children. In case of accidental ingestion, seek professional assistance or contact a poison control center immediately

Directions

Wet hands thoroughly with product and allow to dry without wiping

For children under 6, use only under adult supervision

Not recommended for infants

Other Information

Do not store above 105F

May discolor some fabrics

Harmful to wood finishes and plastics

Inactive Ingredients

Water, Glycerin, PEG-40 Hydrogenated Castor Oil, Carbomer, Triethanolamine, Aloe Barbadensis Leaf Extract, Yellow 5, Red 4